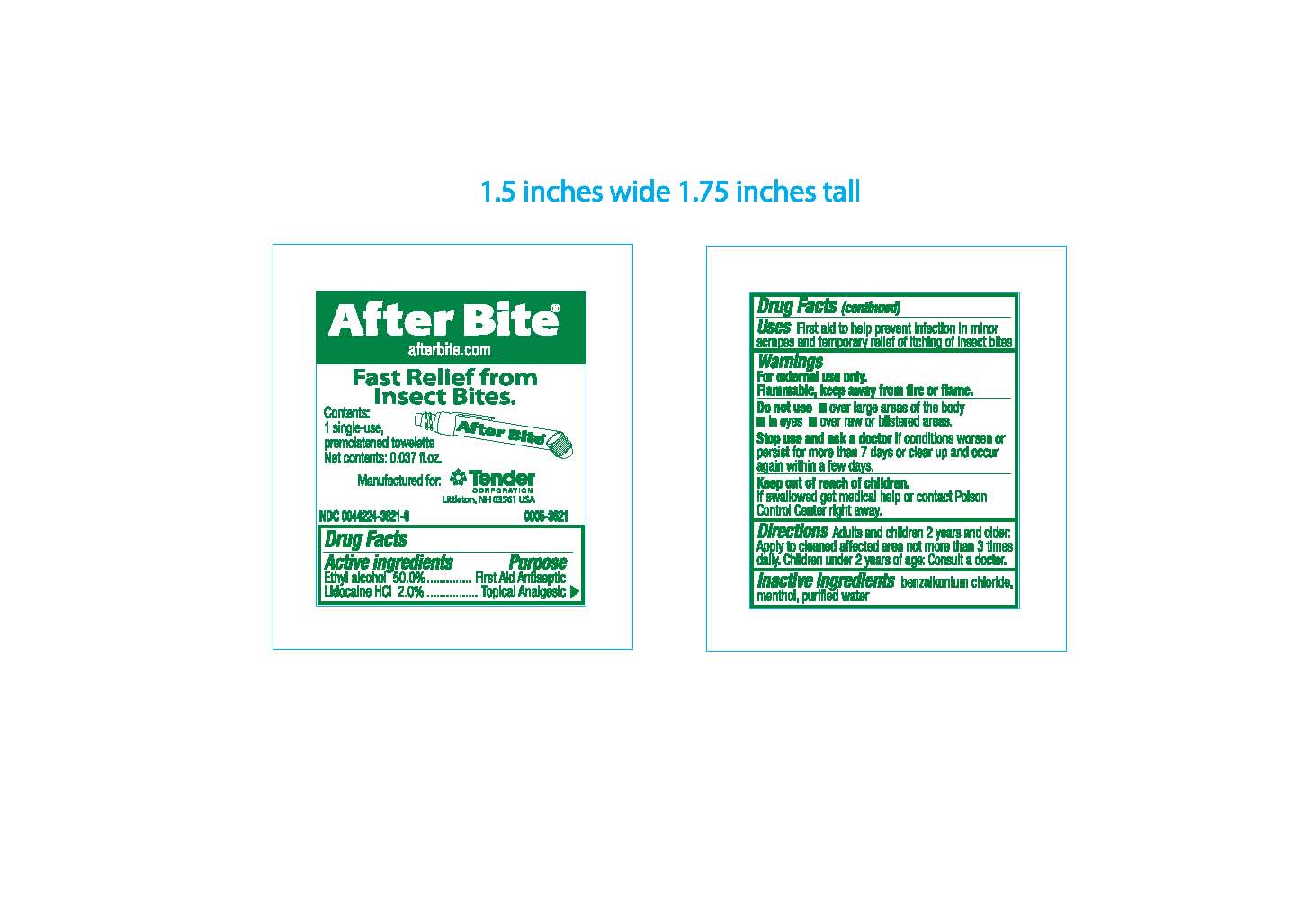 DRUG LABEL: After Bite Wipe
NDC: 44224-3621 | Form: LIQUID
Manufacturer: Tender Corporation
Category: otc | Type: HUMAN OTC DRUG LABEL
Date: 20241227

ACTIVE INGREDIENTS: LIDOCAINE HYDROCHLORIDE 20 mg/1 mL; ALCOHOL 0.5 mL/1 mL
INACTIVE INGREDIENTS: MENTHOL; BENZALKONIUM CHLORIDE; WATER

After Bite Wipe

Active Ingredients

Ethyl Alcohol 50.0%

Lidocaine HCl 2.0%

Purpose

First Aid Antiseptic

Topical Analgesic

Uses

First aid to help prevent infrection in minor scrapes and temporary relief of itching and insect bites

Warnings

For external use only.

Flammable, keep away from fire or flame

Do Not Use

- over large areas of the body
- in eyes
- over raw or blistered areas

Stop use and ask a doctor

if conditions worsen or persist for more than 7 days or clear up and occur again within a few days

Keep out of reach of children

If swallowed get medical kep or contact Poison Control Center right away

Directions

Adults and Children 2 years and older: Apply to cleaned affected area not more than 3 times daily.

Children under 2 years of age: consult a doctor.

Inactive Ingredients

benzalkonium chloride, menthol, purified water

After Bite

Afterbite.com

Fast Relief from Insect Bites.

Contents: 1 single-use, premoistened towelette

Net contents: 0.037fl.oz.

Manufactured for: Tender Corporation Littleton, NH 03561 USA